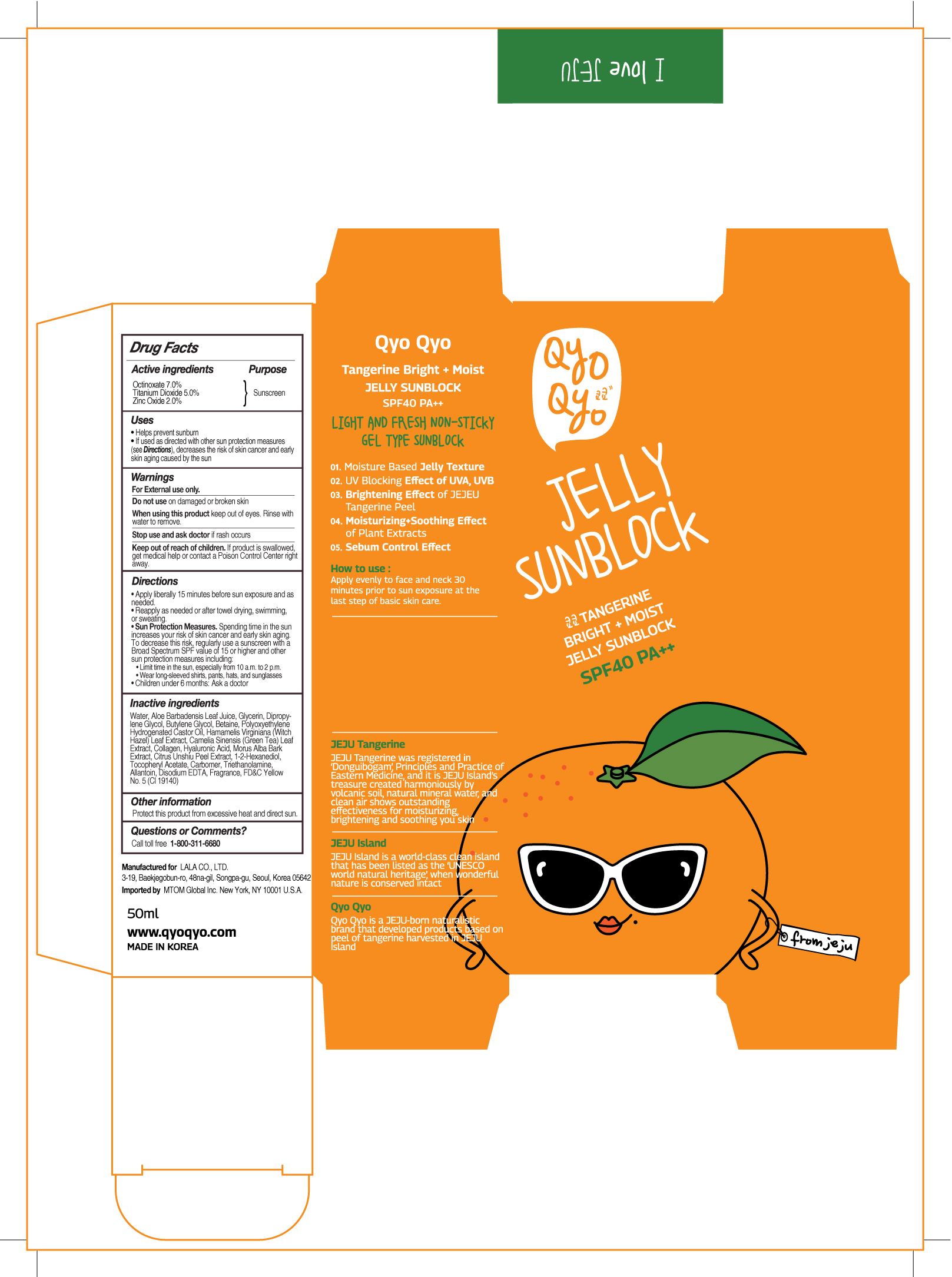 DRUG LABEL: QYO QYO Tangerine Bright Moist Jelly Sunblock SPF 40
NDC: 71733-100 | Form: GEL
Manufacturer: LaLa Co., Ltd.
Category: otc | Type: HUMAN OTC DRUG LABEL
Date: 20180101

ACTIVE INGREDIENTS: TITANIUM DIOXIDE 2.5 g/50 mL; ZINC OXIDE 1 g/50 mL; OCTINOXATE 3.5 g/50 mL
INACTIVE INGREDIENTS: DIPROPYLENE GLYCOL; BUTYLENE GLYCOL; POLYOXYL 40 HYDROGENATED CASTOR OIL; TANGERINE PEEL; ALOE VERA LEAF; HYALURONIC ACID; MORUS ALBA BARK; WATER; BETAINE; HAMAMELIS VIRGINIANA LEAF; CAMELLIA SINENSIS WHOLE; MARINE COLLAGEN, SOLUBLE; 1,2-HEXANEDIOL; TOCOPHEROL; CARBOMER 940; ALLANTOIN; EDETATE DISODIUM; FD&C YELLOW NO. 5; GLYCERIN

ACTIVE INGREDIENTS

OCTINOXATE 7.0%

TITANIUM DIOXIDE 5.0%

ZINC OXIDE 2.0%

PURPOSE

SUNSCREEN

USES

- Helps prevent sunbrun
- If used as directed with other sun protection measures (see Directions), decreases the risk of skin cancer and early skin aging caused by the sun

WARNINGS

For external use only

Do not use on damaged or broken skin

When using this product keep out of eyes. Rinse with water to remove

Stop us and ask doctor if rash occurs

Keep out of reach of children. If product is swallowed, get medical help or contact a Poison Control Center right away.

Directions

- Apply liberally 15 minutes before sun exposure and as needed.
- Reapply as needed or after towel drying, swimming, or sweating.
- Sun Protection Measures. Spending time in the sun increases your risk of skin cancer and early skin aging. To decrease this risk, regularly use a sunscreen with a Broad Spectrum SPF value of 15 or higher and other sun protection measures including:

• Limit time in the sun, especially from 10 a.m. to 2 p.m.
• Wear long-sleeved shirts, pants, hats, and sunglasses

- Children under 6 months: Ask a doctor

Inactive Ingredients

Water, Aloe Barbadensis Leaf Juice, Glycerin, Dipropy- lene Glycol, Butylene Glycol, Betaine, Polyoxyethylene Hydrogenated Castor Oil, Hamamelis Virginiana (Witch Hazel) Leaf Extract, Camelia Sinensis (Green Tea) Leaf Extract, Collagen, Hyaluronic Acid, Morus Alba Bark Extract, Citrus Unshiu Peel Extract, 1-2-Hexanediol, Tocopheryl Acetate, Carbomer, Triethanolamine, Allantoin, Disodium EDTA, Fragrance, FD&C Yellow No. 5 (Cl 19140)

Other Information

Protect this product from excessive heat and direct sun.

Questions or Comments?

Call toll free 1-800-311-6680